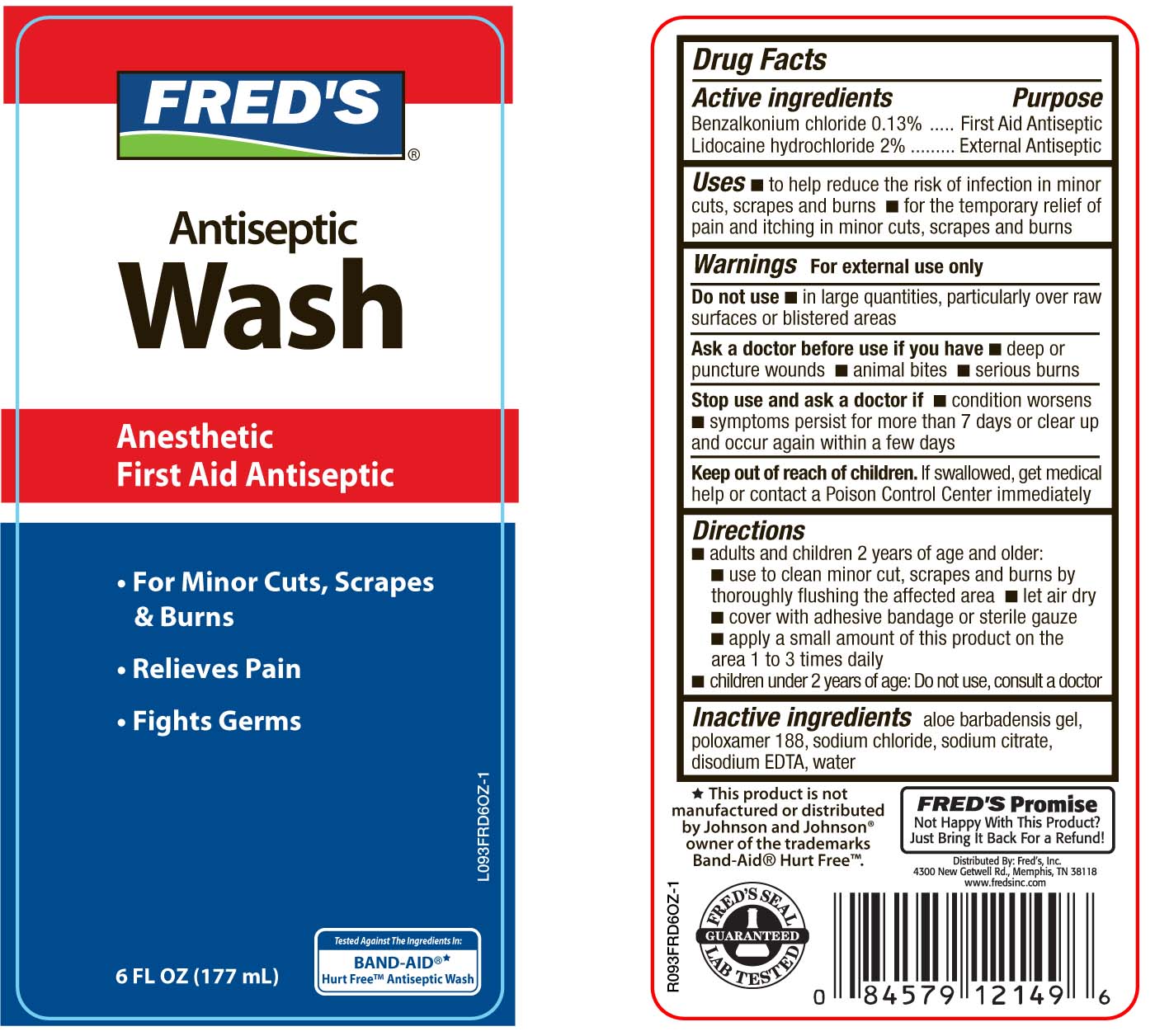 DRUG LABEL: Freds Antiseptic Wash
NDC: 67868-054 | Form: LIQUID
Manufacturer: Pharma Pac, LLC
Category: otc | Type: HUMAN OTC DRUG LABEL
Date: 20100708

ACTIVE INGREDIENTS: BENZALKONIUM CHLORIDE 1.3 mg/1 mL; LIDOCAINE HYDROCHLORIDE 20 mg/1 mL
INACTIVE INGREDIENTS: WATER; POLOXAMER 188; EDETATE DISODIUM; ALOE VERA LEAF; SODIUM CHLORIDE; ANHYDROUS TRISODIUM CITRATE

drug facts

Active ingredient Purpose
Benzalkonium chloride 0.13%..............................First Aid Antiseptic
Lidocaine hydrochloride 2%.................................External Antiseptic

PURPOSE

Uses- to help reduce the risk of infection in minor cuts scrapes and burns
- for the temporary relief of pain and itching associated with minor cuts, scrapes and burns

Keep out of reach of children. If swallowed, get medical help
or contact a Poison Control Center immediately

Uses
- to help reduce the risk of infection in minor cuts scrapes and burns
- for the temporary relief of pain and itching associated with minor cuts, scrapes and burns

Directions

- adults and children 2 years and older:

- use to clean minor cut, scrapes and burns by thoroughly flushing the affected area
- let air dry
- cover with adhesive bandage or sterile gauze
- apply a small amount of this product on the area 1 to 3 times daily

- children under 2 years: Do not use, consult a doctor

Warnings For external use only.
Do not use
- in large quantities, particularly over raw surfaces or blistered areas
Ask a doctor before use if you have - deep or puncture wounds
- animal bites - serious burns
Stop use and ask a doctor if - condition worsens - symptoms
persist for more than 7 days, or clear up and occur again within a few days
Keep out of reach of children. If swallowed, get medical
help or contact a Poison Control Center immediately.

Directions

- adults and children 2 years and older:

- use to clean minor cut, scrapes and burns by thoroughly flushing the affected area
- let air dry
- cover with adhesive bandage or sterile gauze
- apply a small amount of this product on the area 1 to 3 times daily

- children under 2 years: Do not use, consult a doctor

INACTIVE INGREDIENT

Inactive Ingredients aloe barbadensis gel, poloxamer 188, sodium chloride, sodium citrate, disodium EDTA, water